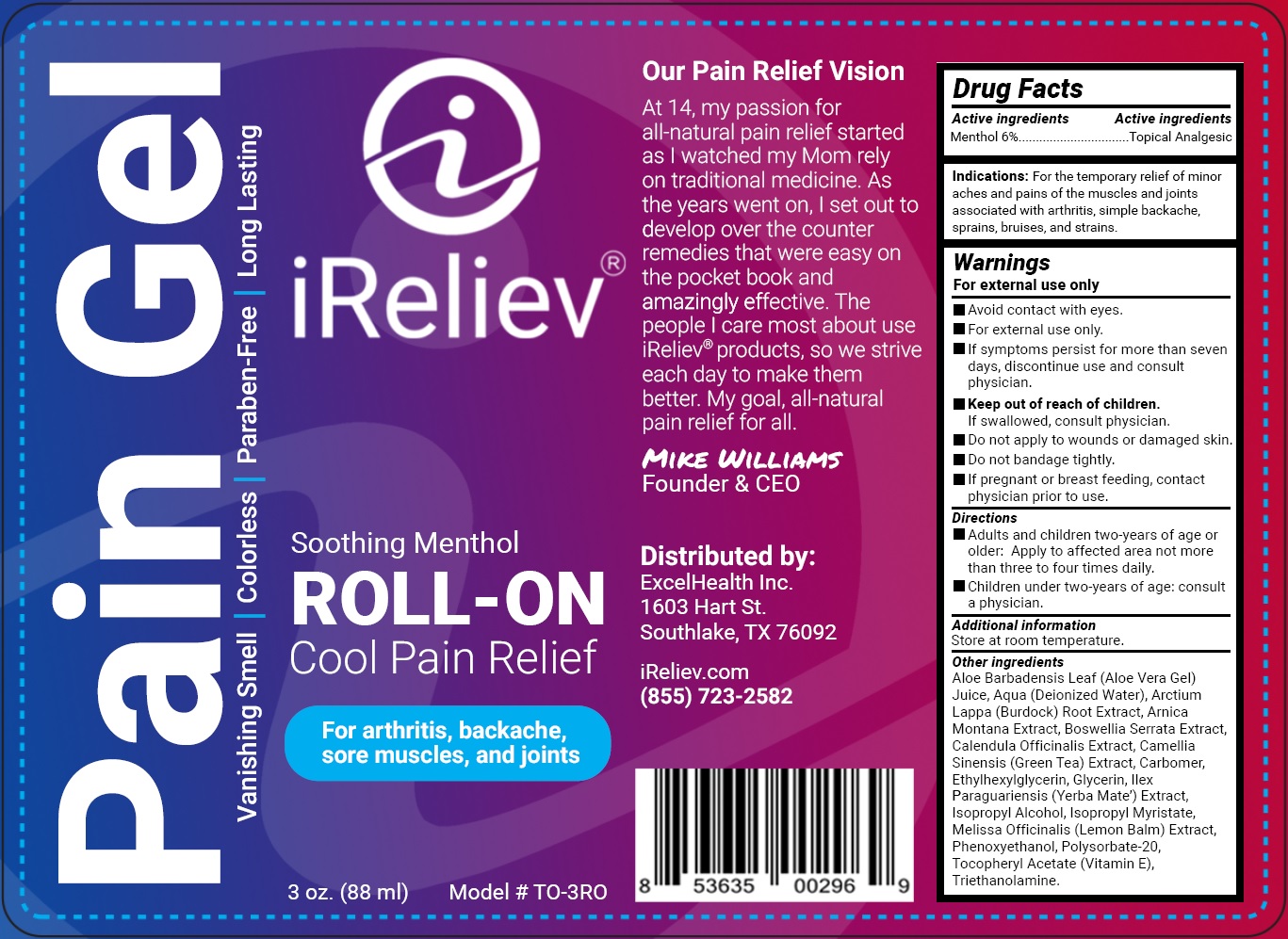 DRUG LABEL: IRELIEV ROLL ON COOL PAIN RELIEF
NDC: 72909-014 | Form: GEL
Manufacturer: Excel Health, Inc
Category: otc | Type: HUMAN OTC DRUG LABEL
Date: 20231105

ACTIVE INGREDIENTS: MENTHOL 60 mg/1 mL
INACTIVE INGREDIENTS: ALOE VERA LEAF; WATER; ARCTIUM LAPPA ROOT; ARNICA MONTANA; CALENDULA OFFICINALIS FLOWER; GREEN TEA LEAF; CARBOXYPOLYMETHYLENE; ETHYLHEXYLGLYCERIN; GLYCERIN; ILEX PARAGUARIENSIS LEAF; ISOPROPYL ALCOHOL; ISOPROPYL MYRISTATE; MELISSA OFFICINALIS; PHENOXYETHANOL; POLYSORBATE 20; .ALPHA.-TOCOPHEROL ACETATE, D-; TROLAMINE

iRELIEVE Roll-On Cool Pain Relief Gel

Active ingredient

Menthol 6%

PURPOSE

Topical Analgesic

Indications:

For the temporary relief of minor aches and pains of the muscles and joints associated with arthritis, simple backache, sprains, bruises, and strains.

Warnings

For external use only

- Avoid contact with eyes
- If symptoms persist for more than seven days, discontinue use and consult physician.

Keep out of reach of children

If swallowed, consult physician

Do not apply

- to wounds or damaged skin
- Do not bandage tightly

If pregnant or breast feeding

contact physician prior to use

Directions

- Adults and children two-years of age or older: Apply to affected area not more than three to four times dail
- Children under two-years of age: consult a physician

Other information

store at room temperature

Inactive Ingredients

Aloe Barbadensis Leaf (Aloe Vera Gel) Juice, Aqua (Deionized Water), Arctium Lappa (Burdock) Root Extract, Arnica Montana Extract, Boswellia Serrata Extract, Calendula Officinalis Extract, Camellia Sinensis (Green Tea) Extract, Carbomer, Ethylhexylglycerin, Glycerin, Ilex Paraguariensis (Yerba Mate’) Extract, Isopropyl Alcohol, Isopropyl Myristate, Melissa Officinalis (Lemon Balm) Extract, Phenoxyethanol, Polysorbate- 20, Tocopheryl Acetate (Vitamin E), Triethanolamine